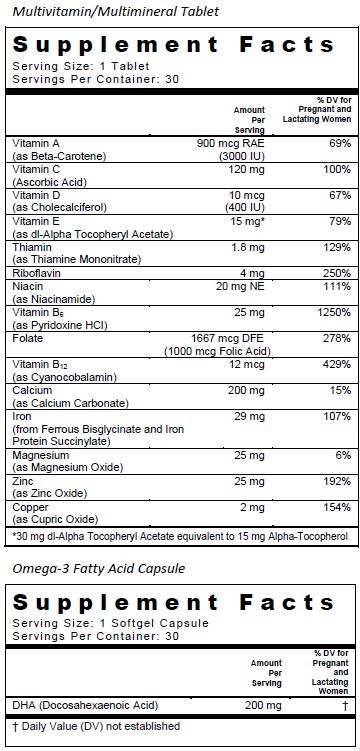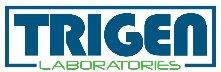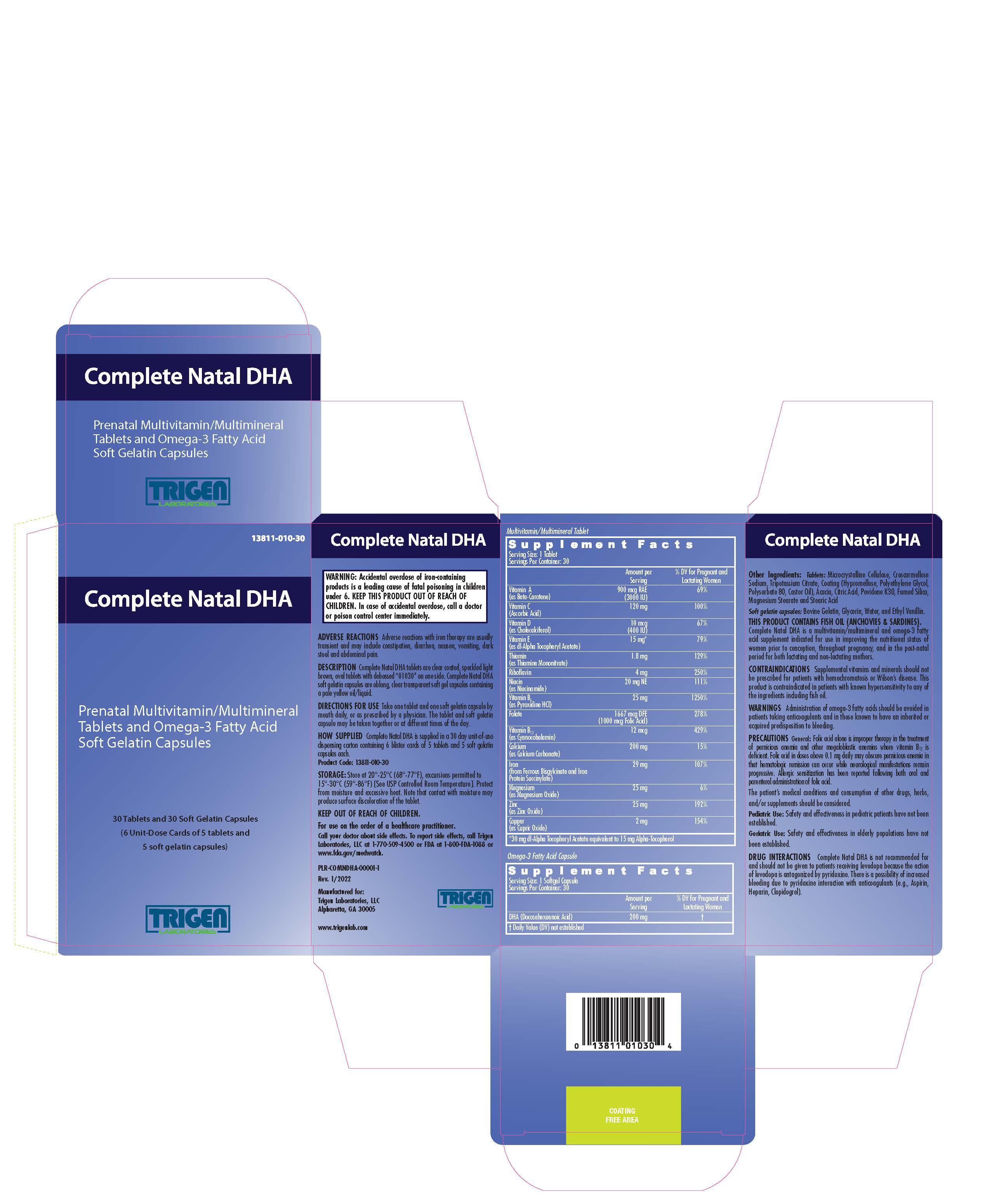 DRUG LABEL: Complete Natal DHA
NDC: 13811-010 | Form: KIT | Route: ORAL
Manufacturer: Trigen Laboratories, LLC
Category: other | Type: DIETARY SUPPLEMENT
Date: 20220126

ACTIVE INGREDIENTS: BETA CAROTENE 3000 [iU]/1 1; Ascorbic Acid 120 mg/1 1; Cholecalciferol 400 [iU]/1 1; .Alpha.-Tocopherol Acetate, DL- 30 mg/1 1; Thiamine Mononitrate 1.8 mg/1 1; Riboflavin 4 mg/1 1; Niacinamide 20 mg/1 1; Pyridoxine Hydrochloride 25 mg/1 1; Folic Acid 1 mg/1 1; Cyanocobalamin 12 ug/1 1; Calcium Carbonate 200 mg/1 1; Ferrous Bisglycinate 29 mg/1 1; Magnesium Oxide 25 mg/1 1; Zinc Oxide 25 mg/1 1; Cupric Oxide 2 mg/1 1; Doconexent 200 mg/1 1
INACTIVE INGREDIENTS: Cellulose, Microcrystalline; CASTOR OIL; Croscarmellose Sodium; Hypromelloses; Acacia; Citric Acid Monohydrate; Povidone K30; Magnesium Stearate; POLYETHYLENE GLYCOL, UNSPECIFIED; Stearic acid; Polysorbate 80; GELATIN TYPE B BOVINE (200 BLOOM); Glycerin; Water; .Alpha.-Tocopherol; Ethyl Vanillin

Complete Natal DHA

SUPPLEMENT FACTS

Other Ingredients:

Tablets: Microcrystalline Cellulose, Croscarmellose Sodium, Tripotassium Citrate, Coating (Hypromellose, Polyethylene Glycol, Polysorbate 80, Castor Oil), Acacia, Citric Acid, Povidone K30, Fumed Silica, Magnesium Stearate and Stearic Acid

Soft gelatin capsules: Bovine Gelatin, Glycerin, Water, and Ethyl Vanillin.

THIS PRODUCT CONTAINS FISH OIL (ANCHOVIES & SARDINES).

Complete Natal DHA is a multivitamin/multimineral and omega-3 fatty acid supplement indicated for use in improving the nutritional status of women prior to conception, throughout pregnancy, and in the post-natal period for both lactating and non-lactating mothers.

CONTRAINDICATIONS

Supplemental vitamins and minerals should not be prescribed for patients with hemochromatosis or Wilson’s disease. This product is contraindicated in patients with known hypersensitivity to any of the ingredients including fish oil.

WARNINGS

Administration of omega-3 fatty acids should be avoided in patients taking anticoagulants and in those known to have an inherited or acquired predisposition to bleeding.

WARNING: Accidental overdose of iron-containing products is a leading cause of fatal poisoning in children under 6. KEEP THIS PRODUCT OUT OF REACH OF CHILDREN. In case of accidental overdose, call a doctor or poison control center immediately.

PRECAUTIONS

General: Folic acid alone is improper therapy in the treatment of pernicious anemia and other megaloblastic anemias where vitamin B12 is deficient. Folic acid in doses above 0.1 mg daily may obscure pernicious anemia in that hematologic remission can occur while neurological manifestations remain progressive. Allergic sensitization has been reported following both oral and parenteral administration of folic acid. The patient’s medical conditions and consumption of other drugs, herbs, and/or supplements should be considered.

Pediatric Use: Safety and effectiveness in pediatric patients have not been established.

Geriatric Use: Safety and effectiveness in elderly populations have not been established.

DRUG INTERACTIONS

Complete Natal DHA is not recommended for and should not be given to patients receiving levodopa because the action of levodopa is antagonized by pyridoxine. There is a possibility of increased bleeding due to pyridoxine interaction with anticoagulants (e.g., Aspirin, Heparin, Clopidogrel).

ADVERSE REACTIONS

Adverse reactions with iron therapy are usually transient and may include constipation, diarrhea, nausea, vomiting, dark stool and abdominal pain.

DESCRIPTION

Complete Natal DHA tablets are clear coated, speckled light brown, oval tablets with debossed "01030" on one side. Complete Natal DHA soft gelatin capsules are oblong, clear transparent soft gel capsules containing a pale yellow oil/liquid.

DIRECTIONS FOR USE

Take one tablet and one soft gelatin capsule by mouth daily, or as prescribed by a physician. The tablet and soft gelatin capsule may be taken together or at different times of the day.

HOW SUPPLIED

Complete Natal DHA is supplied in a 30 day unit-of-use dispensing carton containing 6 blister cards of 5 tablets and 5 soft gelatin capsules each.

Product Code: 13811-010-30

STORAGE

Store at 20°-25°C (68°-77°F), excursions permitted to 15°-30°C (59°-86°F) [See USP Controlled Room Temperature]. Protect from moisture and excessive heat. Note that contact with moisture may produce surface discoloration of the tablet.

KEEP OUT OF REACH OF CHILDREN.

For use on the order of a healthcare practitioner.

Call your doctor about side effects. To report side effects, call Trigen Laboratories, LLC at 1-770-509-4500 or FDA at 1-800-FDA-1088 or www.fda.gov/medwatch.

PLR-COMNDHA-00001-1 Rev. 01/2022

Manufactured for:

Trigen Laboratories, LLC

Alpharetta, GA 30005

www.trigenlab.com

PRINCIPAL DISPLAY PANEL - Kit Carton

TRIGEN
LABORATORIES

13811-010-30

Complete Natal DHA

Prenatal Multivitamin/Multimineral Tablets and Omega-3 Fatty Acid Soft Gelatin Capsules

30 Tablets and 30 Soft Gelatin Capsules

(6 Unit-Dose Cards of 5 tablets and 5 soft gelatin capsules)